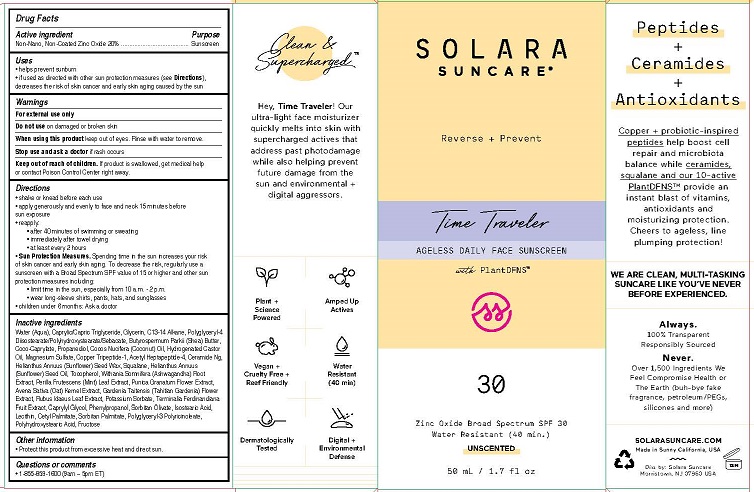 DRUG LABEL: SOLARA SUNCARE - TIME TRAVELER

NDC: 73054-105 | Form: LOTION
Manufacturer: SOLARA SUNCARE, INC.
Category: otc | Type: HUMAN OTC DRUG LABEL
Date: 20251222

ACTIVE INGREDIENTS: ZINC OXIDE 20 g/100 mL
INACTIVE INGREDIENTS: WATER; MEDIUM-CHAIN TRIGLYCERIDES; GLYCERIN; C13-15 ALKANE; POLYGLYCERYL-4 ISOSTEARATE; SHEA BUTTER; COCO-CAPRYLATE; PROPANEDIOL; COCONUT OIL; HYDROGENATED CASTOR OIL; MAGNESIUM SULFATE ANHYDROUS; PREZATIDE COPPER; ACETYL HEXAPEPTIDE-8; CERAMIDE NG; HELIANTHUS ANNUUS SEED WAX; SQUALANE; SUNFLOWER OIL; TOCOPHEROL; WITHANIA SOMNIFERA ROOT; PERILLA FRUTESCENS LEAF; PUNICA GRANATUM FLOWER; OAT; GARDENIA TAITENSIS FLOWER; RUBUS IDAEUS LEAF; POTASSIUM SORBATE; KAKADU PLUM; POLYGLYCERYL-3 RICINOLEATE; POLYHYDROXYSTEARIC ACID (2300 MW); CETYL PALMITATE; SORBITAN MONOPALMITATE; CAPRYLYL GLYCOL; PHENYLPROPANOL; SORBITAN OLIVATE; ISOSTEARIC ACID; LECITHIN, SUNFLOWER; FRUCTOSE

SOLARA (as PLD) -TIME TRAVELER SPF-30 UNSCENTED (73054-105)

ACTIVE INGREDIENTS

Non-Nano, Non-Coated Zinc Oxide 20%

PURPOSE

Sunscreen

USES

- helps prevent sunburn
- if used as directed with other sun protection measures (see Directions), decreases the risk of skin cancer and early skin aging caused by the sun

WARNINGS

For external use only

Do not use on damaged or broken skin

When using this product keep out of eyes. Rinse with water to remove.

Stop use and ask a doctor if rash occurs

Keep out of reach of children. If product is swallowed, get medical help or contact Poison Control Center right away.

DIRECTIONS

- shake or knead before each use
- apply generously and evenly 15 minutes before sun exposure
- reapply:
- after 40 minutes of swimming or sweating
- immediately after towel drying
- at least every 2 hours

- Sun Protection Measures. Spending time in the sun increases your risk of skin cancer and early skin aging. To decrease the risk, regularly use asunscreen with a Broad Spectrum SPF value of 15 or higher and other sun protection measures including:
- limit time in the sun, especially from 10 a.m. - 2 p.m.
- wear long-sleeve shirts, pants, hats, and sunglasses
- children under 6 months: Ask a doctor

INACTIVE INGREDIENTS

Water (Aqua), Caprylic/Capric Triglyceride, Glycerin, C13-14 Alkane, Polyglyceryl-4 Diisostearate/Polyhydroxystearate/Sebacate, Butyrospermum Parkii (Shea) Butter, Coco-Caprylate, Propanediol, Cocos Nucifera (Coconut) Oil, Hydrogenated Castor Oil, Magnesium Sulfate, Copper Tripeptide-1, Acetyl Heptapeptide-4, Ceramide Ng, Helianthus Annuus (Sunflower) Seed Wax, Squalane, Helianthus Annuus (Sunflower) Seed Oil, Tocopherol, Withania Somnifera (Ashwagandha) Root
Extract, Perilla Frutescens (Mint) Leaf Extract, Punica Granatum Flower Extract, Avena Sativa (Oat) Kernel Extract, Gardenia Taitensis (Tahitian Gardenia) Flower Extract, Rubus Idaeus Leaf Extract, Potassium Sorbate, Terminalia Ferdinandiana
Fruit Extract, Caprylyl Glycol, Phenylpropanol, Sorbitan Olivate, Isostearic Acid, Lecithin, Cetyl Palmitate, Sorbitan Palmitate, Polyglyceryl-3 Polyricinoleate, Polyhydroxystearic Acid, Fructose

OTHER INFORMATION

- Protect this product from excessive heat and direct sun.

QUESTIONS OR COMMENTS

- 1-855-859-1600 (9am – 5pm ET)